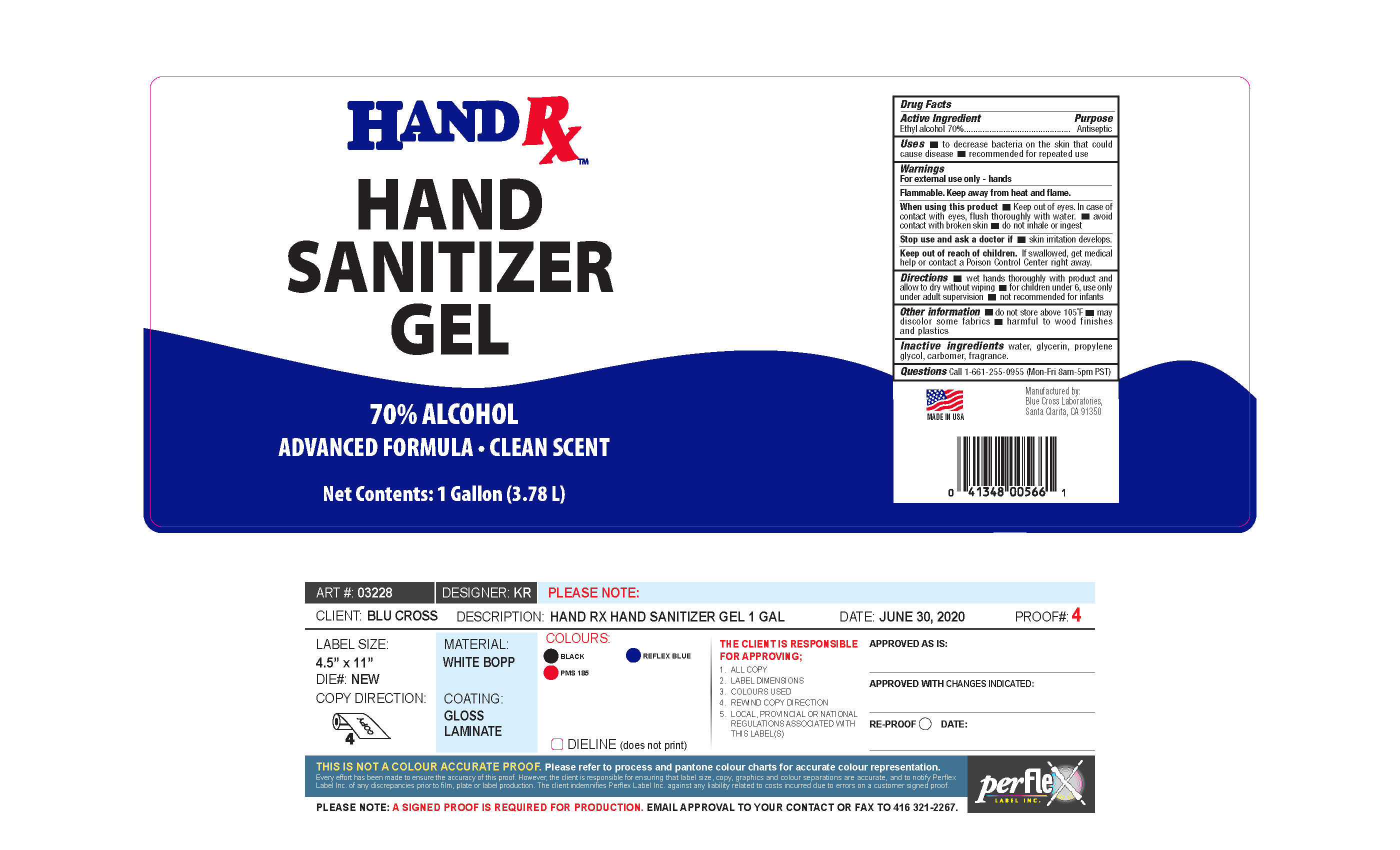 DRUG LABEL: Hand Sanitizer Gel
NDC: 22431-585 | Form: GEL
Manufacturer: Blue Cross Laboratories, Inc.
Category: otc | Type: HUMAN OTC DRUG LABEL
Date: 20200722

ACTIVE INGREDIENTS: ALCOHOL 70 mL/100 L
INACTIVE INGREDIENTS: WATER; GLYCERIN; PROPYLENE GLYCOL; CARBOMER HOMOPOLYMER, UNSPECIFIED TYPE

Hand Rx Hand Sanitizer Gel

Active ingredients purpose

Ethyl Alcohol 70% Antiseptic

Uses

- to decrease bacteria on the skin that could cause disease
- recommended for repeated use

Keep out of reach of children. If swallowed, get medical help or contact a Poison Control Center right away.

Stop use and ask a doctor if

- Skin irritation develops

Warnings

For external use only - hands

Flammable. Keep away from heat flame.

When using this product,

- keep out of eyes. In case of contact with eyes , flush thoroughly with water
- avoid contact with broken skin
- do not inhale or ingest

Directions

- wet hands thoroughly with product and allow to dry without wiping
- for children under 6, use only under adult supervision
- not recommended for infants

Other information

- do not store above 105F
- may discolor some fabrics
- harmful to wood finishes and plastics

INACTIVE INGREDIENT

Inactive ingredients water, glycerin, propylene glycol, carbomer, fragrance

PACKAGE LABEL

Hand Rx

Hand Sanitizer Gel

70% Alcohol

Advanced formula Clean Scent

Net Contents: 1 Gallon (3.78L)

PACKAGE LABEL

Hand Rx

Hand Sanitizer Gel

70% Alcohol

Advanced formula Clean Scent

Net Contents: 1 Gallon (3.78 L)